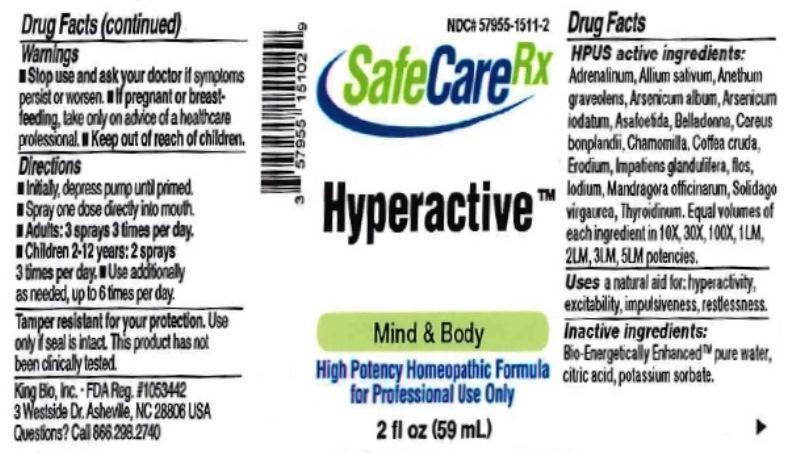 DRUG LABEL: Hyperactive
NDC: 57955-1511 | Form: LIQUID
Manufacturer: King Bio Inc.
Category: homeopathic | Type: HUMAN OTC DRUG LABEL
Date: 20170214

ACTIVE INGREDIENTS: EPINEPHRINE 10 [hp_X]/59 mL; GARLIC 10 [hp_X]/59 mL; DILL 10 [hp_X]/59 mL; ARSENIC TRIOXIDE 10 [hp_X]/59 mL; ARSENIC TRIIODIDE 10 [hp_X]/59 mL; ASAFETIDA 10 [hp_X]/59 mL; ATROPA BELLADONNA 10 [hp_X]/59 mL; HARRISIA POMANENSIS STEM 10 [hp_X]/59 mL; MATRICARIA RECUTITA 10 [hp_X]/59 mL; ARABICA COFFEE BEAN 10 [hp_X]/59 mL; ERODIUM CICUTARIUM 10 [hp_X]/59 mL; IMPATIENS GLANDULIFERA FLOWER 10 [hp_X]/59 mL; IODINE 10 [hp_X]/59 mL; MANDRAGORA OFFICINARUM ROOT 10 [hp_X]/59 mL; SOLIDAGO VIRGAUREA FLOWERING TOP 10 [hp_X]/59 mL; THYROID, UNSPECIFIED 10 [hp_X]/59 mL
INACTIVE INGREDIENTS: WATER; ANHYDROUS CITRIC ACID; POTASSIUM SORBATE

Hyperactive™

ACTIVE INGREDIENT

Drug Facts__________________________________________________________________________________________________________

HPUS active ingredients: Adrenalinum, Allium sativum, Anethum graveolens, Arsenicum album, Arsenicum iodatum, Asafoetida, Belladonna, Cereus bonplandii, Chamomilla, Coffea cruda, Erodium, Impatiens glandulifera, flos, Iodium, Mandragora officinarum, Solidago virgaurea, Thyroidinum. Equal volumes of each ingredient in 10X, 30X, 100X, 1LM, 2LM, 3LM, 5LM potencies.

INDICATIONS AND USAGE

Uses a natural aid for: hyperactivity, excitability, impulsiveness, restlessness.

Inactive Ingredients:

Bio-Energetically Enhanced™ pure water, citric acid and potassium sorbate.

Warnings

- Stop use and ask your doctor if symptoms persist or worsen.
- If pregnant or breast-feeding, take only on advice of a healthcare professional.

- Keep out of reach of children.

Directions

- Initially, depress pump until primed.
- Spray one dose directly into mouth.
- Adults: 3 sprays 3 times per day.
- Children 2-12 years: 2 sprays 3 times per day.
- Use additionally as needed, up to 6 times per day.

OTHER SAFETY INFORMATION

Tamper resistant for your protection. Use only if safety seal is intact. This product has not been clinically tested.

PURPOSE

Uses a natural aid for: hyperactivity, excitability, impulsiveness, restlessness